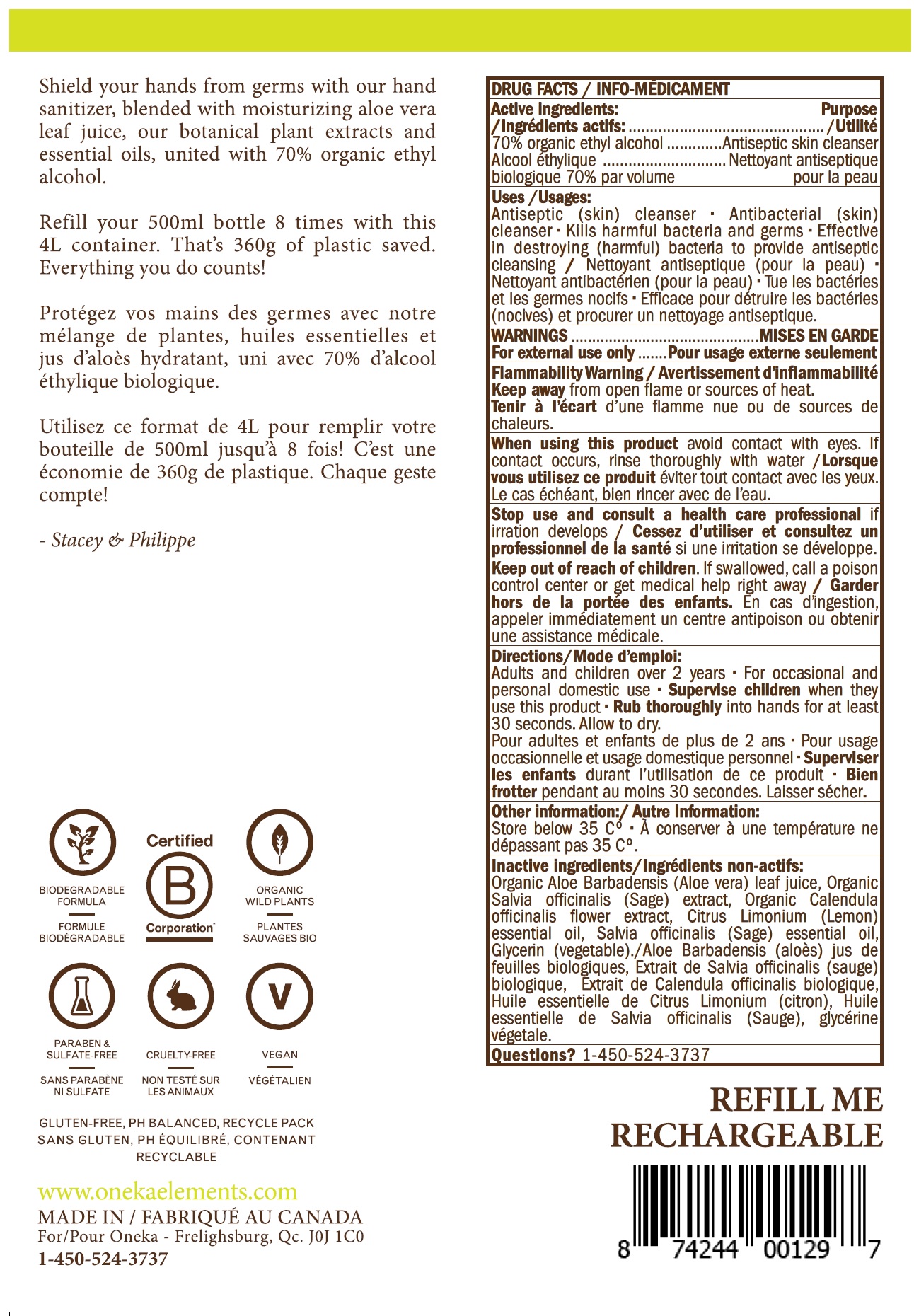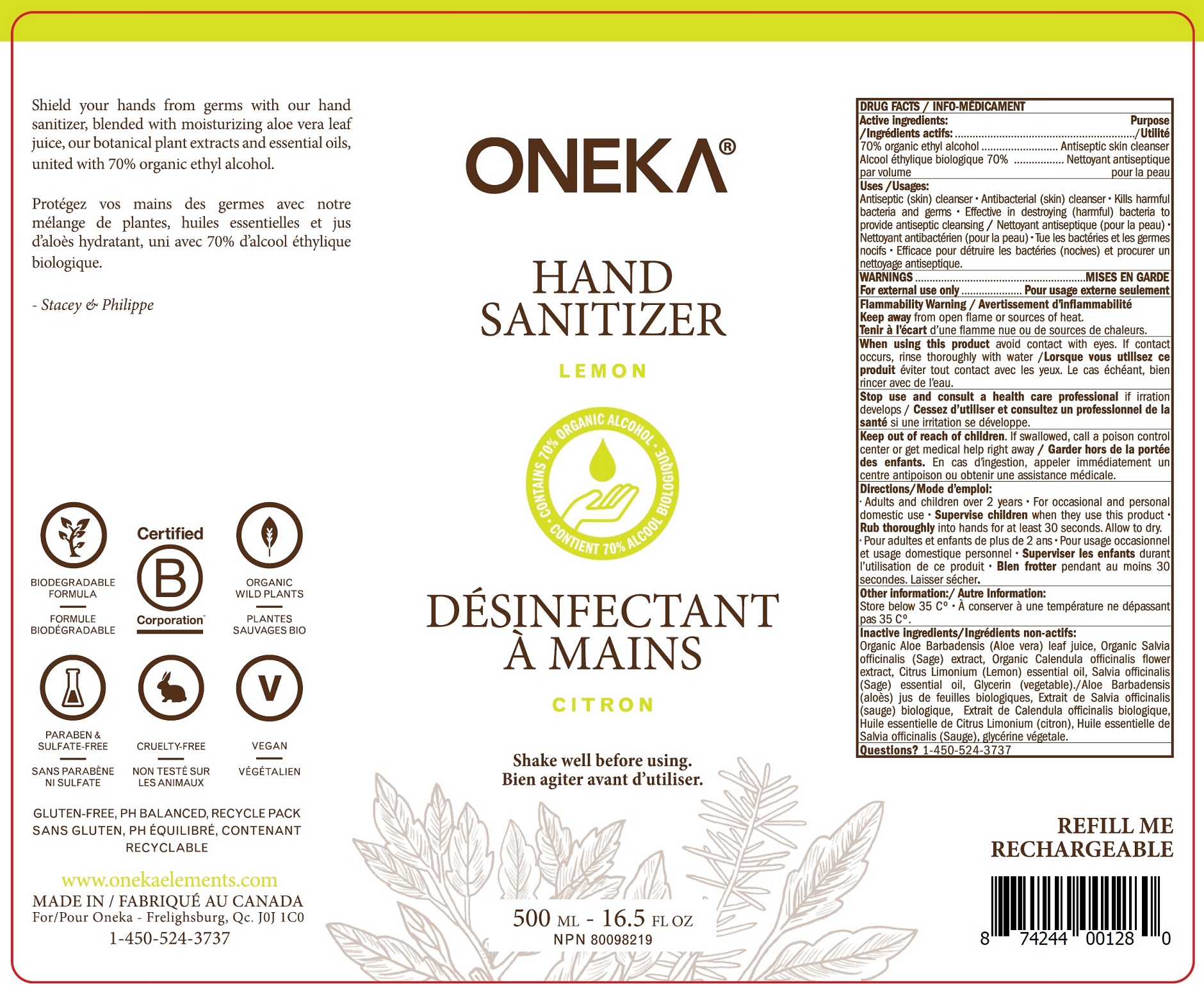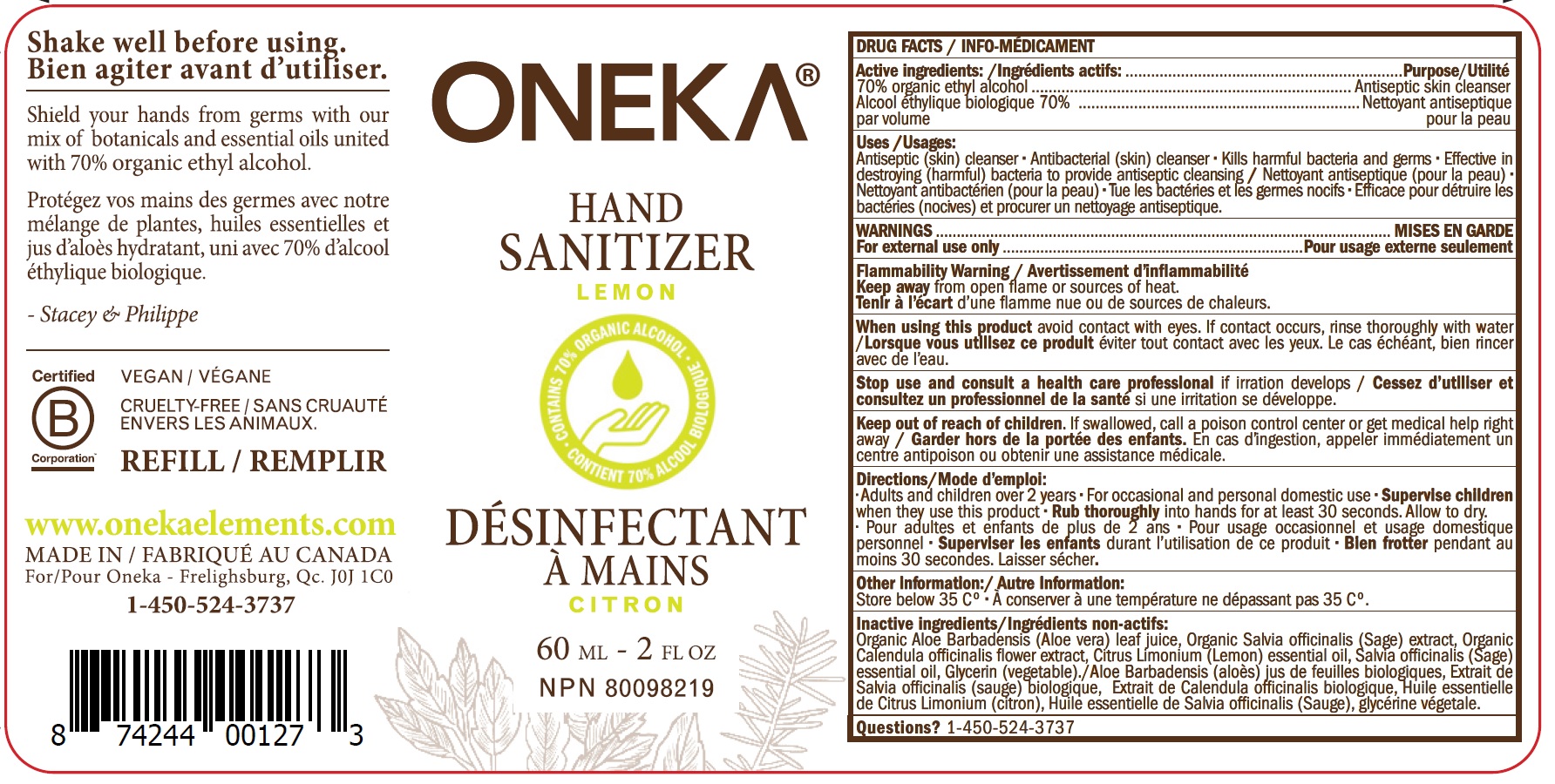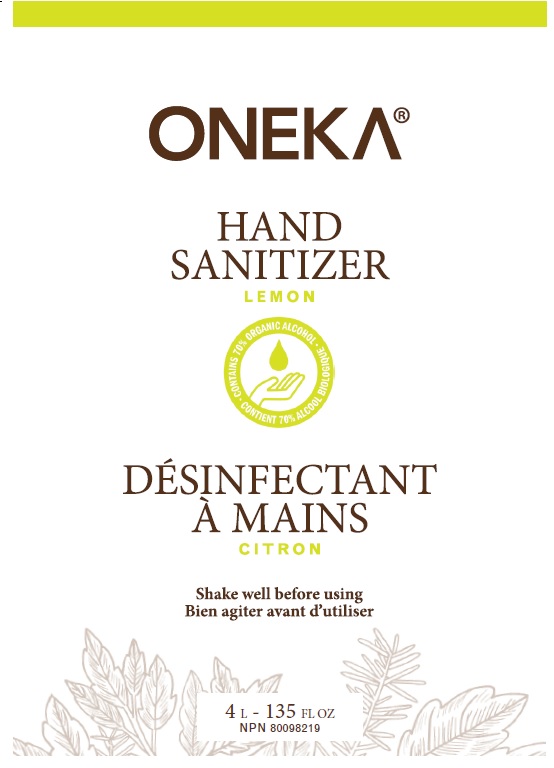 DRUG LABEL: Oneka Hand Sanitizer Lemon
NDC: 81070-100 | Form: LIQUID
Manufacturer: Ecoterre Distribution Inc.
Category: otc | Type: HUMAN OTC DRUG LABEL
Date: 20220107

ACTIVE INGREDIENTS: ALCOHOL 0.7 mL/1 mL
INACTIVE INGREDIENTS: ALOE VERA LEAF; SAGE; CALENDULA OFFICINALIS FLOWER; LEMON; SAGE OIL; GLYCERIN

Oneka Hand Sanitizer Lemon

Active ingredients:

70% organic ethyl alcohol

Purpose

Antiseptic skin cleanser

Uses

Antiseptic (skin) cleanser • Antibacterial (skin) cleanser • Kills harmful bacteria and germs • Effective in destroying (harmful) bacteria to provide antiseptic cleansing

WARNINGS

For external use only

Flammability Warning Keep away from open flame or sources of heat.

When using this product

avoid contact with eyes. If contact occurs, rinse thoroughly with water

Stop use and consult a health care professional

if irritation develops

Keep out of reach of children.

If swallowed, call a poison control center or get medical help right away

Directions

Adults and children over 2 years • For occasional and personal domestic use • Supervise children when they use this product • Rub thoroughly into hands for at least 30 seconds. Allow to dry.

Other information:

Store below 35 Cº

Inactive ingredients

Organic Aloe Barbadensis (Aloe vera) leaf juice, Organic Salvia officinalis (Sage) extract, Organic Calendula officinalis flower extract, Citrus Limonium (Lemon) essential oil, Salvia officinalis (Sage) essential oil, Glycerin (vegetable).

Questions?

1-450-524-3737